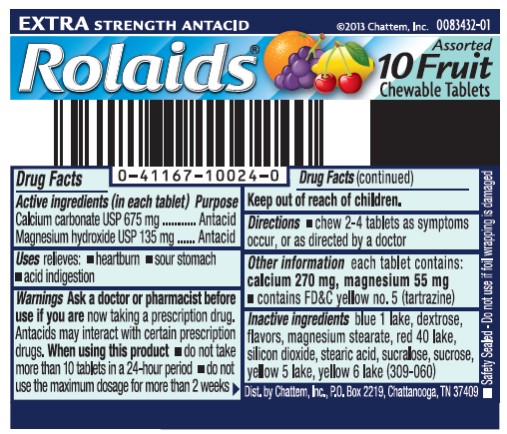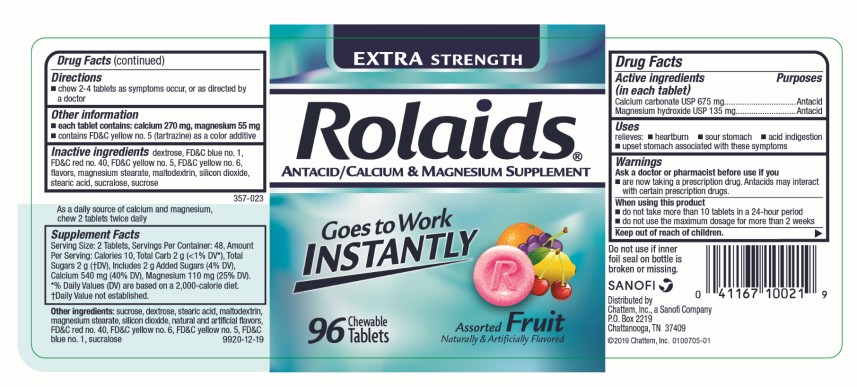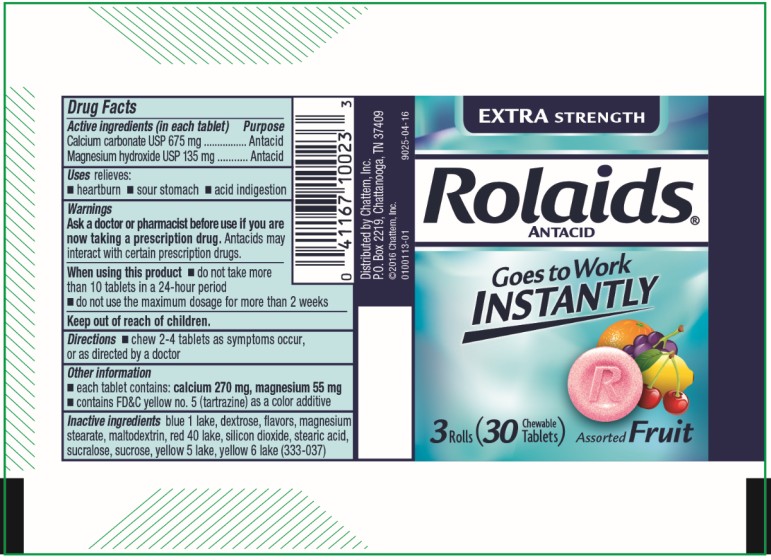 DRUG LABEL: Rolaids Extra Strength Fruit
NDC: 41167-1002 | Form: TABLET, CHEWABLE
Manufacturer: Chattem, Inc.
Category: otc | Type: HUMAN OTC DRUG LABEL
Date: 20260114

ACTIVE INGREDIENTS: CALCIUM CARBONATE 675 mg/1 1; MAGNESIUM HYDROXIDE 135 mg/1 1
INACTIVE INGREDIENTS: FD&C BLUE NO. 1; DEXTROSE; MAGNESIUM STEARATE; FD&C RED NO. 40; SILICON DIOXIDE; STEARIC ACID; SUCRALOSE; SUCROSE; FD&C YELLOW NO. 5; FD&C YELLOW NO. 6; MALTODEXTRIN

Rolaids Extra Strength Tablets Fruit

Extra Strength Antacid Rolaids Assorted Fruit 10 Chewable Tablets

Drug Facts

Active ingredient

(in each tablet)
Calcium carbonate USP 675 mg
Magnesium hydroxide USP 135 mg

Purpose

Antacid

Use

relieves:

- heartburn
- sour stomach
- acid indigestion

Warnings

Ask a doctor or pharmacist before use if you are

now taking a prescription drug. Antacids may interact with certain prescription drugs.

When using this product

- do not take more than 10 tablets in a 24-hour period
- do not use the maximum dosage for more than 2 weeks

Directions

- chew 2-4 tablets as symptoms occur, or as directed by a doctor

Other information

each tablet contains: calcium 270 mg, magnesium 55 mg

- contains FD&C yellow no. 5 (tartrazine)

Inactive ingredients

blue 1 lake, dextrose, flavors, magnesium stearate, red 40 lake, silicon dioxide, stearic acid, sucralose, sucrose, yellow 5 lake, yellow 6 lake (309-060)
Dist. by CHATTEM, INC.
P.O. Box 2219
Chattanooga, TN 37409

Extra Strength Antacid Rolaids Assorted Fruit 96 Chewable Tablets

Drug Facts

Active ingredient

(in each tablet)
Calcium carbonate USP 675 mg
Magnesium hydroxide USP 135 mg

Purpose

Antacid

Use

relieves:

- heartburn
- sour stomach
- acid indigestion

Warnings

Ask a doctor or pharmacist before use if you are

now taking a prescription drug. Antacids may interact with certain prescription drugs.

When using this product

- do not take more than 10 tablets in a 24-hour period
- do not use the maximum dosage for more than 2 weeks

Directions

- chew 2-4 tablets as symptoms occur, or as directed by a doctor

Other information

- each tablet contains: calcium 270 mg, magnesium 55 mg
- contains FD&C yellow no. 5 (tartrazine) as a color additive

Inactive ingredients

blue 1 lake, dextrose, flavors, magnesium stearate, red 40 lake, silicon dioxide, stearic acid, sucralose, sucrose, yellow 5 lake, yellow 6 lake (309-056)

As a daily source of calcium and magnesium, chew 2 tablets twice daily.

Supplement Facts
Serving Size: 2 Tablets, Servings Per Container: 48, Amount Per Serving: Calories 8, Total Carb 2 g (<1% DV*), Sugars 2 g (†DV), Calcium 540 mg (54% DV), Magnesium 110 mg (29% DV). *Percent Daily Values (DV) are based on a 2,000 calories diet.
†Daily Value not established.

Other ingredients

sucrose, dextrose, stearic acid, magnesium stearate, silicon dioxide, natural and artificial flavors, red 40 lake, yellow 6 lake, yellow 5 lake, blue 1 lake, sucralose

Extra Strength Antacid Rolaids Assorted Fruit 30 Chewable Tablets

Drug Facts

Active ingredient

(in each tablet)
Calcium carbonate USP 675 mg
Magnesium hydroxide USP 135 mg

Purpose

Antacid

Use

relieves:

- heartburn
- sour stomach
- acid indigestion

Warnings

Ask a doctor or pharmacist before use if you are

now taking a prescription drug. Antacids may interact with certain prescription drugs.

When using this product

- do not take more than 10 tablets in a 24-hour period
- do not use the maximum dosage for more than 2 weeks

Directions

- chew 2-4 tablets as symptoms occur, or as directed by a doctor

Other information

- each tablet contains: calcium 270 mg, magnesium 55 mg
- contains FD&C yellow no. 5 (tartrazine) as a color additive

Inactive ingredients

blue 1 lake, dextrose, flavors, magnesium stearate, red 40 lake, silicon dioxide, stearic acid, sucralose, sucrose, yellow 5 lake, yellow 6 lake (309-060)
Dist. by CHATTEM, INC.
P.O. Box 2219
Chattanooga, TN 37409

PRINCIPAL DISPLAY PANEL

EXTRA STRENGTH ANTACID
Rolaids®
10 Assorted Fruit Chewable Tablets

PRINCIPAL DISPLAY PANEL

EXTRA STRENGTH
Rolaids®
ANTACID/ CALCIUM & MAGNESIUM SUPPLEMENT
Goes to Work
INSTANTLY
96 Chewable Tablets
Assorted Fruit

PRINCIPAL DISPLAY PANEL

EXTRA STRENGTH
Rolaids®
ANTACID
Rapid Relief of:
Heartburn
Acid Indigestion
3 Rolls
30 Chewable Tablets
Assorted Fruit